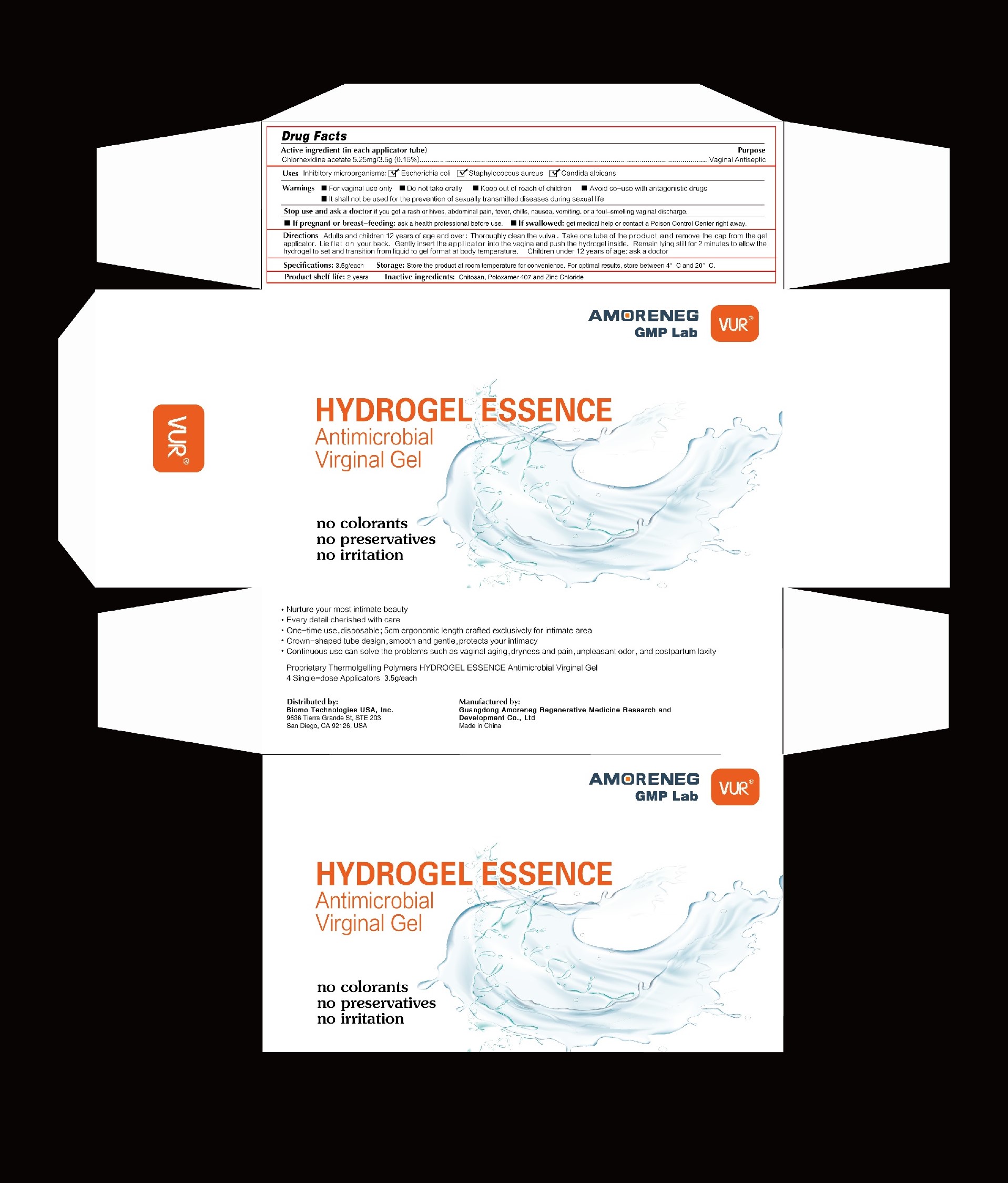 DRUG LABEL: HYDROGEL ESSENCE Antimicrobial Virginal Gel.
NDC: 84642-001 | Form: GEL
Manufacturer: Guangdong Amoreneg Medicine Research and Development Co., LTD
Category: otc | Type: HUMAN OTC DRUG LABEL
Date: 20240815

ACTIVE INGREDIENTS: CHLORHEXIDINE ACETATE 5.25 mg/3.5 g
INACTIVE INGREDIENTS: ZINC CHLORIDE; POLIGLUSAM; POLOXAMER 407

84642-001 (HYDROGEL ESSENCE Antimicrobial Virginal Gel)

Active ingredient

Chlorhexidine acetate 0.15%

Purpose

Vaginal Antiseptic

Use

Inhibitory microorganisms: Escherichia coli, Staphylococcus aureus, Candida albican

Warnings

■ For vaginal use only;

■ Do not take orally;

■ Avoid co-use with antagonistic drugs;

■ It shall not be used for the prevention of sexually transmitted diseases during sexual life.

Stop use and ask a doctor

if you get a rash or hives, abdominal pain,fever, chills, nausea, vomiting, or a foul-smelling vaginal discharge.

If pregnant or nreast-feeding

ask a health professional before use.

Keep out of reach of children.

If swallowed, get medical help or contact a Poison Control Center right away.

Directions

Aduits and children 12 years of age and over: Thoroughly clean the vulva.Take one tube of the product and remove the cap from the gel applicator. Lie flat on your back. Gently insert the applicator into the vagina and push the hydrogel inside. Remain lying still for 2 minutes to allow the hydrogel to set and transition from liquid to gel format at body temperature.Children under 12 years of age: ask a doctor

Storage

Store the product at room temperature for convenience.
For optimail results, store between 4°C and 20°C

Inactive ingredients

Chitosan, Poloxamer 407 and Zinc Chloride